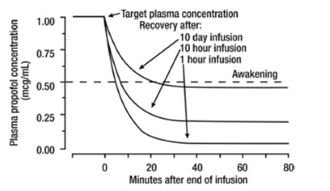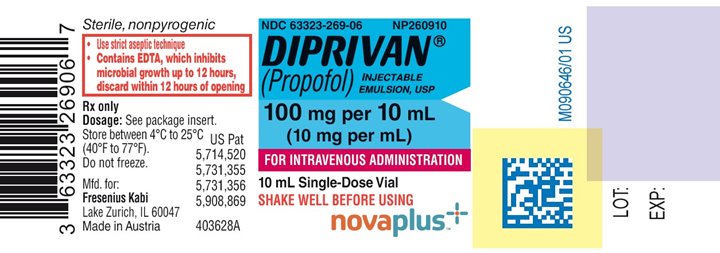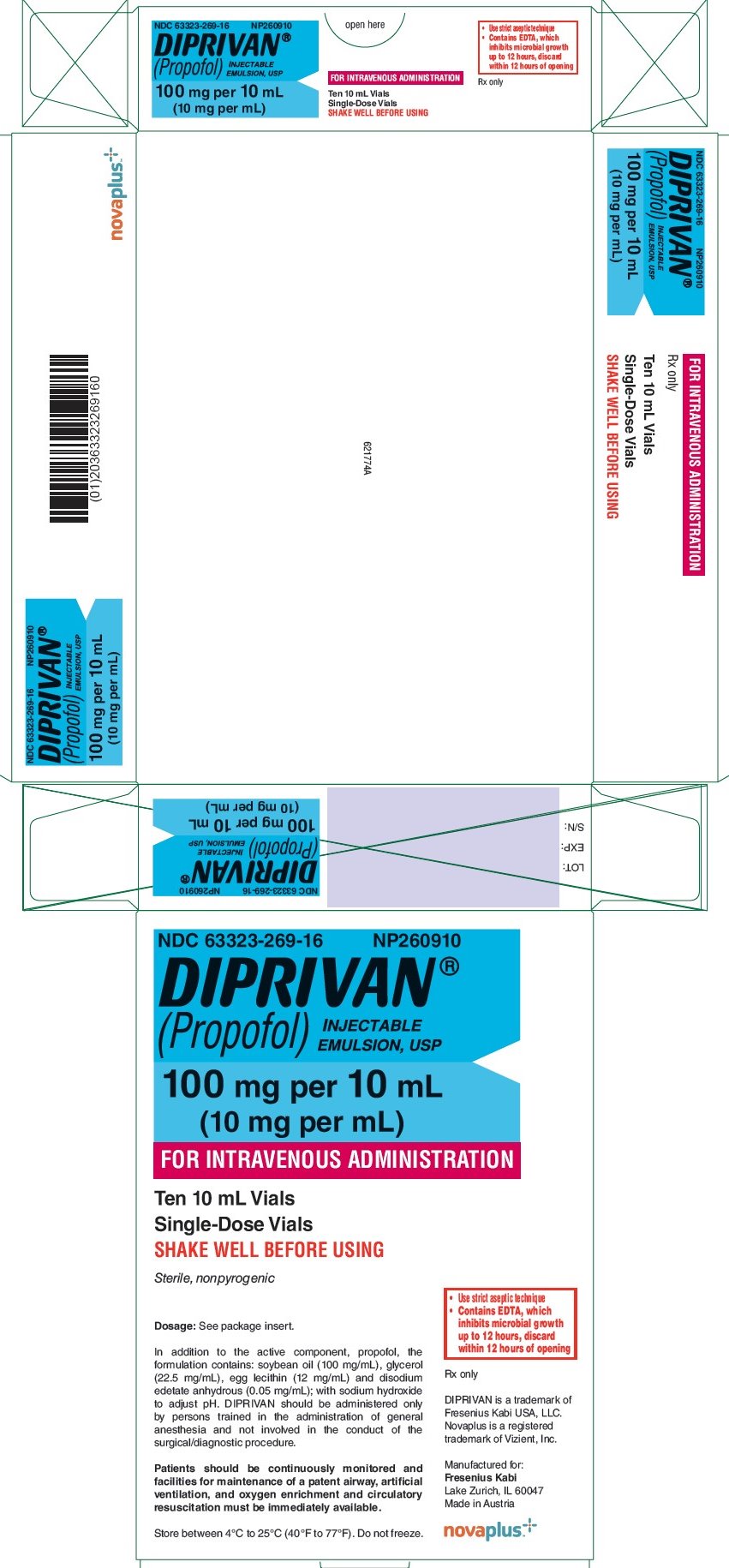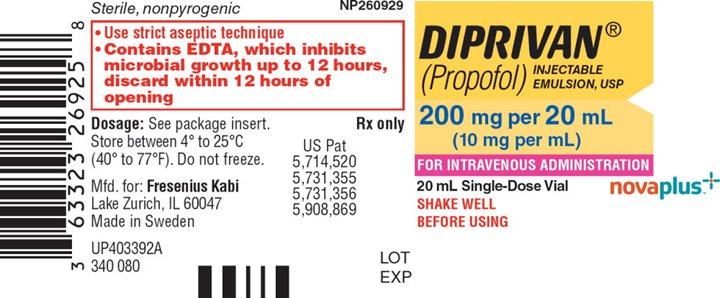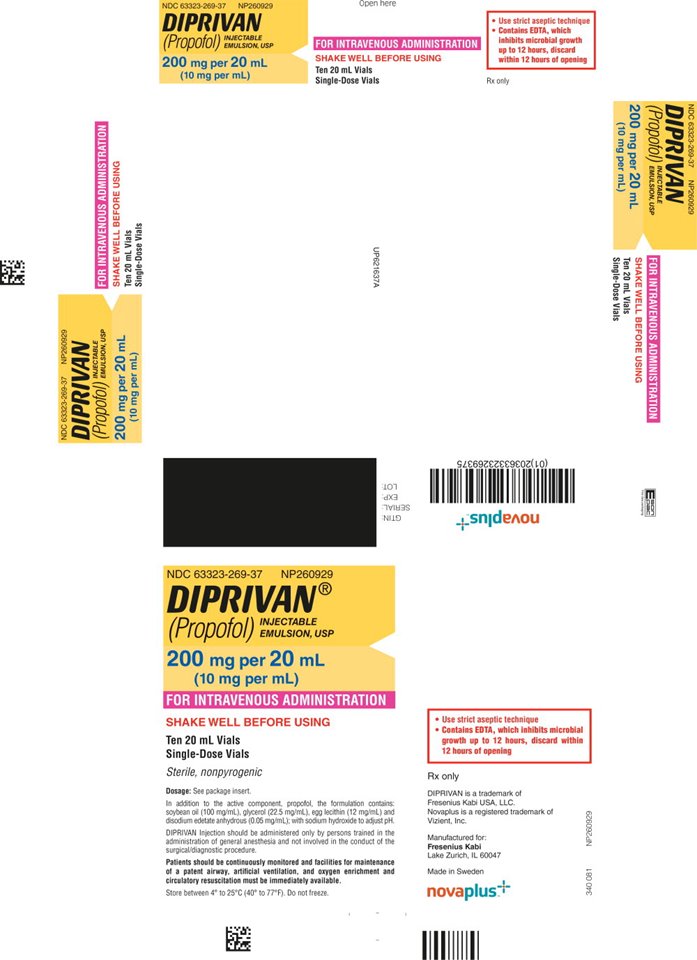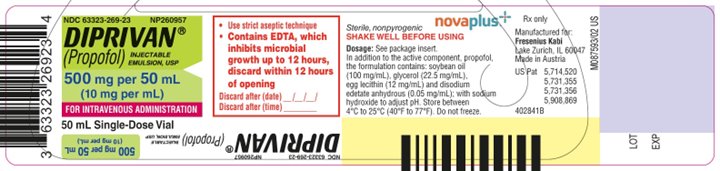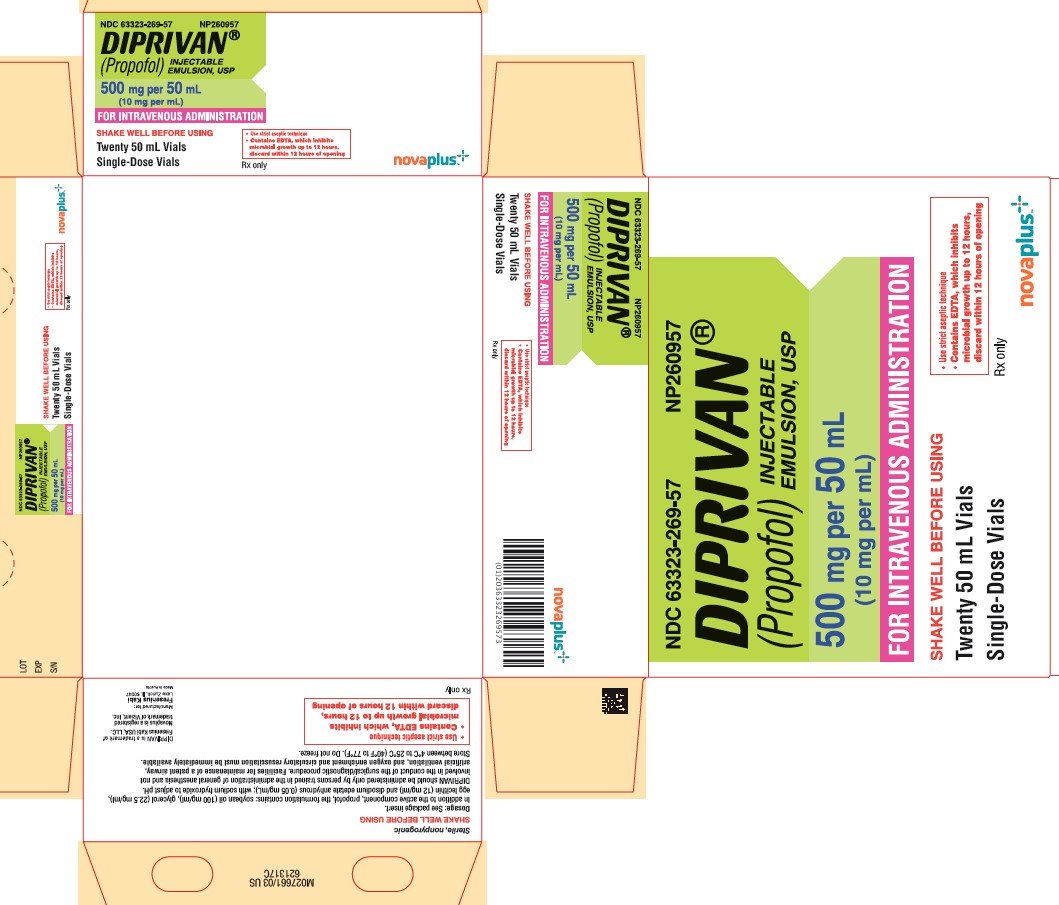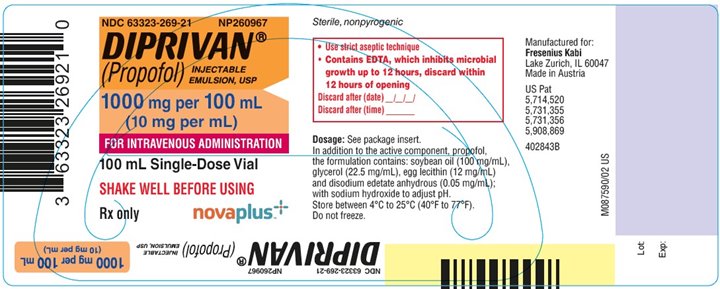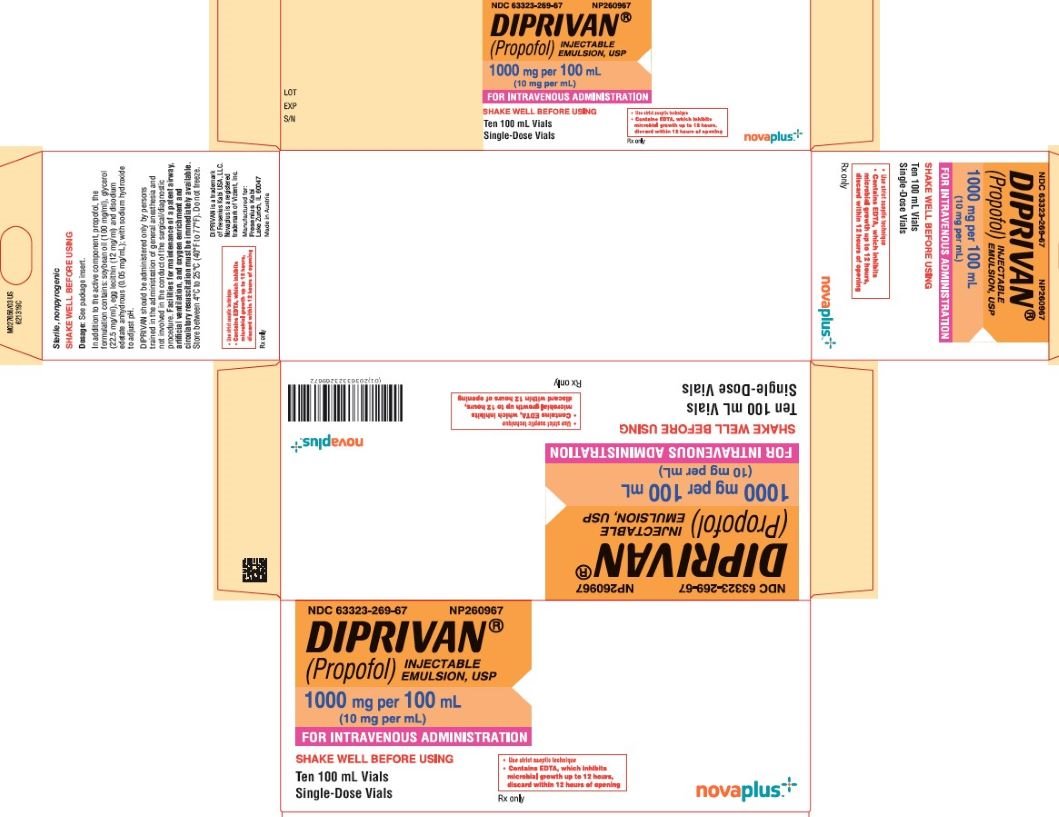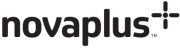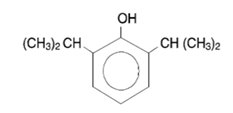 DRUG LABEL: Diprivan
NDC: 63323-269 | Form: INJECTION, EMULSION
Manufacturer: Fresenius Kabi USA, LLC
Category: prescription | Type: HUMAN PRESCRIPTION DRUG LABEL
Date: 20250911

ACTIVE INGREDIENTS: PROPOFOL 10 mg/1 mL
INACTIVE INGREDIENTS: SOYBEAN OIL 100 mg/1 mL; GLYCERIN 22.5 mg/1 mL; EGG PHOSPHOLIPIDS 12 mg/1 mL; EDETATE DISODIUM ANHYDROUS; SODIUM HYDROXIDE

HIGHLIGHTS OF PRESCRIBING INFORMATION

These highlights do not include all the information needed to use DIPRIVAN safely and effectively. See full prescribing information for DIPRIVAN.
DIPRIVAN® (propofol injectable emulsion), for intravenous use Initial U.S. Approval: 1991

1 INDICATIONS AND USAGE

DIPRIVAN is an intravenous general anesthetic and sedation drug indicated for:

- Induction of General Anesthesia for Patients Greater than or Equal to 3 Years of Age
- Maintenance of General Anesthesia for Patients Greater than or Equal to 2 Months of Age
- Initiation and Maintenance of Monitored Anesthesia Care (MAC) Sedation in Adult Patients
- Sedation for Adult Patients in Combination with Regional Anesthesia
- Intensive Care Unit (ICU) Sedation of Intubated, Mechanically Ventilated Adult Patients

Limitations of Use:

DIPRIVAN is not recommended for induction of anesthesia below the age of 3 years or for maintenance of anesthesia below the age of 2 months.
MAC sedation in the pediatric population is not recommended. DIPRIVAN is not indicated for use in Pediatric ICU sedation.

2 DOSAGE AND ADMINISTRATION

See Full Prescribing Information for detailed dosing instructions.

3 DOSAGE FORMS AND STRENGTHS

Injectable emulsion: 100 mg per 10 mL (10 mg/mL), 200 mg per 20 mL (10 mg/mL), 500 mg per 50 mL (10 mg/mL), and 1,000 mg per 100 mL (10 mg/mL) single-dose vials (3)

4 CONTRAINDICATIONS

Known hypersensitivity to propofol, egg or soybean. (4)

5 WARNINGS AND PRECAUTIONS

Hypersensitivity Reactions: Serious and sometimes fatal reactions. (5.1)

Microbial Contamination: Strict aseptic technique must be maintained during handling. DIPRIVAN vials are never to be accessed more than once or used on more than one person. Administration should commence promptly and be completed within 12 hours after the vial has been opened. Discard unused drug product. Do not use if contamination is suspected. (5.2)

Cardiovascular depression: Cases of bradycardia, asystole, and cardiac arrest have been reported. Pediatric patients are susceptible to this effect, particularly when fentanyl is given concomitantly. (5.4)

6 ADVERSE REACTIONS

The most common adverse reactions >1% were bradycardia, arrhythmia, tachycardia, hypotension, hypertension, decreased cardiac output, movement, apnea, respiratory acidosis during weaning, rash, pruritus, burning/stinging or pain at injection site, and hyperlipemia. (6)

To report SUSPECTED ADVERSE REACTIONS, contact Fresenius Kabi USA at 1-800-551-7176 or FDA at 1-800-FDA-1088 or www.fda.gov/medwatch.

7 DRUG INTERACTIONS

Opioids, Sedatives or Other Analgesic Agents: May increase the anesthetic/sedative and cardiorespiratory effects. (7)

Valproate: May lead to increased blood levels of propofol. (7)

FULL PRESCRIBING INFORMATION

1 INDICATIONS AND USAGE

DIPRIVAN is an intravenous general anesthetic and sedation drug indicated for:

- Induction of General Anesthesia for Patients Greater than or Equal to 3 Years of Age
- Maintenance of General Anesthesia for Patients Greater than or Equal to 2 Months of Age
- Initiation and Maintenance of Monitored Anesthesia Care (MAC) Sedation in Adult Patients
- Sedation for Adult Patients in Combination with Regional Anesthesia
- Intensive Care Unit (ICU) Sedation of Intubated, Mechanically Ventilated Adult Patients

Limitations of Use

DIPRIVAN is not recommended for induction of anesthesia below the age of 3 years or for maintenance of anesthesia below the age of 2 months because its safety and effectiveness have not been established in those populations [see Pediatric Use (8.4)].

Safety, effectiveness and dosing guidelines for DIPRIVAN have not been established for MAC sedation in the pediatric population; therefore, it is not recommended for this use [see Pediatric Use (8.4)].

DIPRIVAN is not indicated for use in Pediatric ICU sedation since the safety of this regimen has not been established [see Pediatric Use (8.4)].

2 DOSAGE AND ADMINISTRATION

2.1 Important Dosage and Administration Information

Parenteral drug products should be inspected visually for particulate matter and discoloration prior to administration whenever solution and container permit.

Shake well before use. Do not use if there is evidence of excessive creaming or aggregation, if large droplets are visible, or if there are other forms of phase separation indicating that the stability of the product has been compromised. Slight creaming, which should disappear after shaking, may be visible upon prolonged standing. Do not use if there is evidence of separation of the phases of the emulsion.

DIPRIVAN with EDTA inhibits microbial growth for up to 12 hours, as demonstrated by test data for representative USP microorganisms. Product is packaged under nitrogen.

For general anesthesia or monitored anesthesia care (MAC) sedation, DIPRIVAN should be administered only by persons trained in the administration of general anesthesia and not involved in the conduct of the surgical/diagnostic procedure. Sedated patients should be continuously monitored, and equipment for maintaining a patent airway, providing artificial ventilation, administering supplemental oxygen, and instituting cardiovascular resuscitation must be immediately available. Patients should be continuously monitored for early signs of hypotension, apnea, airway obstruction, and/or oxygen desaturation. These cardiorespiratory effects are more likely to occur following rapid bolus administration, especially in the elderly, debilitated, or ASA-PS III or IV patients.

For sedation of intubated, mechanically ventilated adult patients in the Intensive Care Unit, DIPRIVAN should be administered only by persons skilled in the management of critically ill patients and trained in cardiovascular resuscitation and airway management.

Guidelines for Aseptic Technique for General Anesthesia/MAC Sedation

DIPRIVAN must be prepared for use just prior to initiation of each individual anesthetic/sedative procedure. The vial rubber stopper should be disinfected using 70% isopropyl alcohol. DIPRIVAN should be drawn into a sterile syringe immediately after a vial is opened. When withdrawing DIPRIVAN from vials, a sterile vent spike should be used. The syringe should be labelled with appropriate information including the date and time the vial was opened. Administration should commence promptly and be completed within 12 hours after the vial has been opened.

DIPRIVAN must be prepared for single dose only. Any unused DIPRIVAN drug product, reservoirs, dedicated administration tubing and/or solutions containing DIPRIVAN must be discarded at the end of the anesthetic procedure or at 12 hours, whichever occurs sooner. The intravenous line should be flushed every 12 hours and at the end of the anesthetic procedure to remove residual DIPRIVAN. [see Warnings and Precautions (5.2)].

Guidelines for Aseptic Technique for ICU Sedation

DIPRIVAN must be prepared for single dose only. Strict aseptic techniques must be followed. The vial rubber stopper should be disinfected using 70% isopropyl alcohol. A sterile vent spike and sterile tubing must be used for administration of DIPRIVAN. As with other lipid emulsions, the number of intravenous line manipulations should be minimized. Administration should commence promptly and must be completed within 12 hours after the vial has been spiked. The tubing and any unused DIPRIVAN drug product must be discarded after 12 hours.

If DIPRIVAN is transferred to a syringe prior to administration, it should be drawn into a sterile syringe immediately after a vial is opened. When withdrawing DIPRIVAN from a vial, a sterile vent spike should be used. The syringe should be labelled with appropriate information including the date and time the vial was opened. Administration should commence promptly and be completed within 12 hours after the vial has been opened. DIPRIVAN should be discarded and administration lines changed after 12 hours. [see Warnings and Precautions (5.2)]

Administration with Lidocaine

If lidocaine is to be administered to minimize pain on injection of DIPRIVAN, it is recommended that it be administered prior to DIPRIVAN administration or that it be added to DIPRIVAN immediately before administration and in quantities not exceeding 20 mg lidocaine/200 mg DIPRIVAN. [see Warnings and Precautions (5.13)]

Compatibility and Stability

DIPRIVAN should not be mixed with other therapeutic agents prior to administration.

Dilution Prior to Administration

DIPRIVAN is provided as a ready-to-use formulation. However, should dilution be necessary, it should only be diluted with 5% Dextrose Injection, USP, and it should not be diluted to a concentration less than 2 mg/mL because it is an emulsion. In diluted form it has been shown to be more stable when in contact with glass than with plastic (95% potency after 2 hours of running infusion in plastic).

Administration with Other Fluids

Compatibility of DIPRIVAN with the coadministration of blood/serum/plasma has not been established [see Warnings and Precautions (5.15)].

When administered using a y-type infusion set, DIPRIVAN has been shown to be compatible with the following intravenous fluids:

- 5% Dextrose Injection, USP
- Lactated Ringers Injection, USP
- Lactated Ringers and 5% Dextrose Injection
- 5% Dextrose and 0.45% Sodium Chloride Injection, USP
- 5% Dextrose and 0.2% Sodium Chloride Injection, USP.

Administration with Pumps

When administering DIPRIVAN by infusion, syringe or volumetric pumps are recommended to provide controlled infusion rates. When infusing DIPRIVAN to patients undergoing magnetic resonance imaging, metered control devices may be utilized if mechanical pumps are impractical.

Administration with Filters

Clinical experience with the use of in-line filters and DIPRIVAN during anesthesia or ICU/MAC sedation is limited. DIPRIVAN should only be administered through a filter with a pore size of 5 micron or greater unless it has been demonstrated that the filter does not restrict the flow of DIPRIVAN and/or cause the breakdown of the emulsion. Filters should be used with caution and where clinically appropriate. Continuous monitoring is necessary due to the potential for restricted flow and/or breakdown of the emulsion.

2.2 Induction of General Anesthesia for Patients Greater than or Equal to 3 Years of Age

Adult Patients

Most adult patients under 65 years of age and classified as ASA-PS I or II require 2 mg/kg to 2.5 mg/kg of DIPRIVAN. For induction, whether administered by infusion or intravenous injection the dose of DIPRIVAN to the patient should be titrated against the response of the patient and until there are clinical signs consistent with the onset of anesthesia. As with other sedative-hypnotic agents, the amount of intravenous opioid and/or benzodiazepine premedication may impact the dose of DIPRIVAN required for induction of general anesthesia.

Elderly, Debilitated, or ASA-PS III or IV Patients

Due to the reduced clearance and higher blood concentrations, most elderly, debilitated, or ASA-PS III or IV patients require approximately 1 mg/kg to 1.5 mg/kg of DIPRIVAN for induction of anesthesia. For induction, whether administered by infusion or intravenous injection the dose administration of DIPRIVAN to the patient should be titrated against the response of the patient and until there are clinical signs consistent with the onset of anesthesia. A rapid bolus may increase the likelihood of undesirable cardiorespiratory depression. [see Warnings and Precautions (5.12)]

Pediatric Patients

Most patients aged 3 years through 16 years and classified ASA-PS I or II require 2.5 mg/kg to 3.5 mg/kg of DIPRIVAN for induction. Within this dosage range, younger pediatric patients may require higher induction doses than older pediatric patients. As with other sedative-hypnotic agents, the amount of intravenous opioid and/or benzodiazepine premedication may impact the dose of DIPRIVAN required for induction of general anesthesia. A lower dosage is recommended for pediatric patients classified as ASA-PS III or IV. Boluses of DIPRIVAN may be administered via small veins if pretreated with lidocaine or via antecubital or larger veins [see Dosage and Administration (2.7)].

Neurosurgical Patients

Most adult neurosurgical patients require 1 mg/kg to 2 mg/kg of DIPRIVAN. Slower induction is recommended to allow for titration to achieve an adequate clinical response [see Warnings and Precautions (5.6)]. Whether administered by infusion or an intravenous injection, the dose of DIPRIVAN to the patient should be titrated against the response of the patient and until there are clinical signs consistent with the onset of anesthesia.

Cardiac Anesthesia

Most adult cardiac patients require 0.5 mg/kg to 1.5 mg/kg of DIPRIVAN. Slower induction is recommended to allow for titration to clinical response and to prevent hemodynamic instability. Whether administered by infusion or intravenous injection, the dose of DIPRIVAN to the patient should be titrated against the response of the patient until the clinical signs show the onset of anesthesia. Other agents used in addition to DIPRIVAN for induction and maintenance of anesthesia may require DIPRIVAN doses to be titrated to ensure adequate sedation level.

DIPRIVAN has been well-studied in patients with coronary artery disease and in patients with hemodynamically significant valvular or congenital heart disease. No significant safety issues or changes to the induction of anesthesia is generally required for these patient groups. Dosing should be titrated based on depth of anesthesia.

As with other anesthetic and sedative-hypnotic agents, DIPRIVAN in healthy patients causes a decrease in blood pressure that is secondary to decreases in preload (ventricular filling volume at the end of the diastole) and afterload (arterial resistance at the beginning of the systole). The magnitude of these changes is proportional to the blood and effect site concentrations achieved. These concentrations depend upon the dose and speed of the induction and maintenance infusion rates.

In addition, lower heart rates are observed during maintenance with DIPRIVAN, possibly due to reduction of the sympathetic activity and/or resetting of the baroreceptor reflexes. Therefore, anticholinergic agents should be administered when increases in vagal tone are anticipated.

As with other anesthetic agents, DIPRIVAN reduces myocardial oxygen consumption.

Further studies are needed to confirm and delineate the extent of these effects on the myocardium and the coronary vascular system.

Morphine premedication (0.15 mg/kg) with nitrous oxide 67% in oxygen has been shown to decrease the necessary DIPRIVAN maintenance infusion rates and therapeutic blood concentrations when compared to non-narcotic (lorazepam) premedication. The rate of DIPRIVAN administration should be determined based on the patient's premedication and adjusted according to clinical responses.

2.3 Maintenance of General Anesthesia for Patients Greater than or Equal to 2 Months of Age

DIPRIVAN has been used with a variety of agents commonly used in anesthesia such as atropine, scopolamine, glycopyrrolate, diazepam, depolarizing and nondepolarizing muscle relaxants, and opioid analgesics, as well as with inhalational and regional anesthetic agents.

In the elderly, debilitated, or ASA-PS III or IV patients, rapid bolus doses should not be used, as this will increase the likelihood of undesirable cardiorespiratory depression.

Adult Patients

In adults, anesthesia can be maintained by administering DIPRIVAN by infusion or intermittent intravenous bolus injection. The patient's clinical response will determine the infusion rate or the amount and frequency of incremental injections

Continuous Infusion

DIPRIVAN 100 mcg/kg/min to 200 mcg/kg/min administered in a variable rate infusion with 60% to 70% nitrous oxide and oxygen provides anesthesia for patients undergoing general surgery. Maintenance by infusion of DIPRIVAN should immediately follow the induction dose in order to provide satisfactory or continuous anesthesia during the induction phase. During this initial period following the induction dose, higher rates of infusion are generally required (150 mcg/kg/min to 200 mcg/kg/min) for the first 10 minutes to 15 minutes. Infusion rates should subsequently be decreased 30% to 50% during the first half-hour of maintenance. Generally, rates of 50 mcg/kg/min to 100 mcg/kg/min in adults should be achieved during maintenance in order to optimize recovery times.

Other drugs that cause CNS depression (hypnotics/sedatives, inhalational anesthetics, and opioids) can increase the CNS depression induced by propofol.

Intermittent Bolus

Increments of DIPRIVAN 25 mg (2.5 mL) to 50 mg (5 mL) may be administered in adult patients undergoing general surgery. The incremental boluses should be administered when changes in vital signs indicate a response to surgical stimulation or light anesthesia.

Cardiac Anesthesia

The maintenance dose of propofol in adult cardiac patients should be administered as 25 to 100 mcg/kg/min, and should be adjusted according to the patient’s sedation level and clinical response.

Pediatric Patients

In children greater than or equal to 2 months of age, anesthesia can be maintained by administering DIPRIVAN by infusion or intermittent intravenous bolus injection. An initial bolus of between 1-4 mg/kg, followed by subsequent administration of smaller aliquots based on patients’ response (0.5 – 2 mg/kg). The patient's clinical response will determine the infusion rate or the amount and frequency of incremental injections.

Continuous Infusion

DIPRIVAN administered as a variable rate infusion provides satisfactory anesthesia for most children 2 months of age or older, ASA-PS I or II, undergoing general anesthesia.

In general, for the pediatric population, maintenance by infusion of DIPRIVAN at a rate of 200 mcg/kg/min to 300 mcg/kg/min should immediately follow the induction dose. Following the first half-hour of maintenance, infusion rates of 125 mcg/kg/min to 150 mcg/kg/min are typically needed. DIPRIVAN should be titrated to achieve the desired clinical effect. Younger pediatric patients may require higher maintenance infusion rates than older pediatric patients [see Clinical Studies (14.1)].

Intermittent Bolus

An initial bolus of 1-4 mg/kg should be administered, with additional 0.5 to 2 mg/kg doses as needed. The incremental boluses should be administered when changes in vital signs indicate a response to surgical stimulation or light anesthesia.

2.4 Initiation and Maintenance of Monitored Anesthesia Care (MAC) Sedation in Adult Patients

When DIPRIVAN is administered for MAC sedation, rates of administration should be individualized and titrated to clinical response. In most patients, the rates of DIPRIVAN administration will be in the range of 25 mcg/kg/min to 75 mcg/kg/min.

During initiation of MAC sedation, slow infusion or slow injection techniques are preferable over rapid bolus administration. During maintenance of MAC sedation, a variable rate infusion is preferable over intermittent bolus dose administration. In the elderly, debilitated, or ASA-PS III or IV patients, rapid (single or repeated) bolus dose administration should not be used for MAC sedation [see Warnings and Precautions (5.12)]. A rapid bolus injection may result in undesirable cardiorespiratory depression.

Initiation of MAC Sedation in Adult Patients

For initiation of MAC sedation, either an infusion or a slow injection method may be utilized while closely monitoring cardiorespiratory function. With the infusion method, sedation may be initiated by infusing DIPRIVAN at 100 mcg/kg/min to 150 mcg/kg/min (6 mg/kg/hour to 9 mg/kg/hour) for a period of 3 minutes to 5 minutes and titrating to the desired clinical effect while closely monitoring respiratory function. With the slow injection method for initiation, patients will require approximately 0.5 mg/kg administered over 3 minutes to 5 minutes and titrated to clinical responses. When DIPRIVAN is administered slowly over 3 minutes to 5 minutes, most patients will be adequately sedated, and the peak drug effect can be achieved while minimizing undesirable cardiorespiratory effects occurring at high plasma levels.

In the elderly, debilitated, or ASA-PS III or IV patients, rapid (single or repeated) bolus dose administration should not be used for MAC sedation [see Warnings and Precautions (5.12)]. The rate of administration should be over 3 minutes to 5 minutes and the dosage of DIPRIVAN should be reduced to approximately 80% of the usual adult dosage in these patients according to their condition, responses, and changes in vital signs.

Maintenance of MAC Sedation in Adult Patients

For maintenance of sedation, a variable rate infusion method is preferable over an intermittent bolus dose method.

With the variable rate infusion method, patients will generally require maintenance rates of 25 mcg/kg/min to 75 mcg/kg/min (1.5 mg/kg/hour to 4.5 mg/kg/hour) during the first 10 minutes to 15 minutes of sedation maintenance. Infusion rates should subsequently be decreased over time to 25 mcg/kg/min to 50 mcg/kg/min and adjusted to clinical responses. In titrating to clinical effect, allow approximately 2 minutes for onset of peak drug effect.

Infusion rates should always be titrated downward in the absence of clinical signs of light sedation until mild responses to stimulation are obtained in order to avoid sedative administration of DIPRIVAN at rates higher than are clinically necessary.

If the intermittent bolus dose method is used, increments of DIPRIVAN 10 mg (1 mL) or 20 mg (2 mL) can be administered and titrated to desired clinical effect. With the intermittent bolus method of sedation maintenance, there is increased potential for respiratory depression, transient increases in sedation depth, and prolongation of recovery.

In the elderly, debilitated, or ASA-PS III or IV patients, rapid (single or repeated) bolus dose administration should not be used for MAC sedation [see Warnings and Precautions (5.12)]. The rate of administration and the dosage of DIPRIVAN should be reduced to approximately 80% of the usual adult dosage in these patients according to their condition, responses, and changes in vital signs.

DIPRIVAN can be administered as the sole agent for maintenance of MAC sedation during surgical/diagnostic procedures. When DIPRIVAN sedation is supplemented with opioid and/or benzodiazepine medications, these agents increase the sedative and respiratory effects of DIPRIVAN and may also result in a slower recovery profile [see Drug Interactions (7)].

2.5 Clinical Responses and Dose Titrations

Changes in vital signs indicating a stress response to surgical stimulation or the emergence from anesthesia may be controlled by the administration of 25 mg (2.5 mL) to 50 mg (5 mL) incremental boluses and/or by increasing the infusion rate of DIPRIVAN.

For minor surgical procedures (e.g., body surface) nitrous oxide (60% to 70%) can be combined with a variable rate DIPRIVAN infusion to provide satisfactory anesthesia. With more stimulating surgical procedures (e.g., intra-abdominal), or if supplementation with nitrous oxide is not provided, administration rate(s) of DIPRIVAN and/or opioids should be increased in order to provide adequate anesthesia.

Infusion rates should always be titrated downward in the absence of clinical signs of light anesthesia in order to avoid administration of DIPRIVAN at rates higher than are clinically necessary. Generally, rates of 50 mcg/kg/min to 100 mcg/kg/min in adults should be achieved during maintenance in order to optimize recovery times.

Other drugs that cause CNS depression (hypnotics/sedatives, inhalational anesthetics, and opioids) can increase CNS depression induced by propofol. Morphine premedication (0.15 mg/kg) with nitrous oxide 67% in oxygen has been shown to decrease the necessary propofol injection maintenance infusion rate and therapeutic blood concentrations when compared to non-narcotic (lorazepam) premedication.

Propofol blood concentrations at steady-state are generally proportional to infusion rates, especially in individual patients. Undesirable effects such as cardiorespiratory depression are likely to occur at higher blood concentrations which result from bolus dosing or rapid increases in the infusion rate. An adequate interval (3 minutes to 5 minutes) must be allowed between dose adjustments to allow for and assess the clinical effects.

2.6 Intensive Care Unit (ICU) Sedation of Intubated, Mechanically Ventilated Adult Patients

In the Intensive Care Unit (ICU), DIPRIVAN can be administered to intubated, mechanically ventilated adult patients to provide continuous sedation and control of stress responses only by persons skilled in the medical management of critically ill patients and trained in cardiovascular resuscitation and airway management.

DIPRIVAN should be individualized according to the patient's condition and response, blood lipid profile, and vital signs [see Warnings and Precautions (5.8, 5.9, and 5.10)]. For intubated, mechanically ventilated adult patients, Intensive Care Unit (ICU) sedation should be initiated slowly with a continuous infusion in order to titrate to desired clinical effect and minimize hypotension. When indicated, initiation of sedation should begin at 5 mcg/kg/min (0.3 mg/kg/hour). The infusion rate should be increased by increments of 5 mcg/kg/min to 10 mcg/kg/min (0.3 mg/kg/hour to 0.6 mg/kg/hour) until the desired level of sedation is achieved. A minimum period of 5 minutes between adjustments should be allowed for onset of peak drug effect.

Most adult ICU patients recovering from the effects of general anesthesia or deep sedation will require maintenance rates of 5 mcg/kg/min to 50 mcg/kg/min (0.3 mg/kg/hour to 3 mg/kg/hour) titrated to desired level of clinical response. With medical ICU patients or patients who have recovered from the effects of general anesthesia or deep sedation, the rate of administration of 50 mcg/kg/min or higher may be required to achieve adequate sedation. These higher rates of administration may increase the likelihood of patients developing hypotension. Administration should not exceed 4 mg/kg/hour unless the benefits outweigh the risks [see Warnings and Precautions (5.8)].

Dosage and rate of administration should be individualized and titrated to the desired effect, according to clinically relevant factors including the patient’s underlying medical problems, preinduction and concomitant medications, age, ASA-PS classification, and level of debilitation of the patient. The elderly, debilitated, and ASA-PS III or IV patients may have exaggerated hemodynamic and respiratory responses to rapid bolus doses [see Warnings and Precautions (5.12)].

Dosages of DIPRIVAN should be reduced in patients who have received large dosages of opioids. The DIPRIVAN dosage requirement may also be reduced by adequate management of pain with analgesic agents. As with other sedative medications, there is interpatient variability in dosage requirements, and these requirements may change with time [see Dosage and Administration (2.6)].

Evaluation of level of sedation and assessment of CNS function should be carried out daily throughout maintenance to determine the minimum dose of DIPRIVAN required for sedation [see Clinical Studies (14.4)]. Bolus administration of 10 mg or 20 mg should only be used to rapidly increase depth of sedation in patients where hypotension is not likely to occur. Patients with compromised myocardial function, intravascular volume depletion, or abnormally low vascular tone (e.g., sepsis) may be more susceptible to hypotension [see Warnings and Precautions (5.4)].

Abrupt discontinuation of DIPRIVAN prior to weaning or for daily evaluation of sedation levels should be avoided [see Warnings and Precautions (5.8)].

2.7 Summary of Dosage Guidelines

Dosages and rates of administration in the following table should be individualized and titrated to clinical response. Safety and dosing requirements for induction of anesthesia in pediatric patients have only been established for children 3 years of age or older. Safety and dosing requirements for the maintenance of anesthesia have only been established for children 2 months of age and older.

Table 1. Summary of Dosage Guidelines for Different Indications
INDICATION | DOSAGE AND ADMINISTRATION
Induction of General Anesthesia: | Healthy Adults Less Than 65 Years of Age: 2 mg/kg to 2.5 mg/kg until induction onset, as determined by clinical response of the patient.; Elderly, Debilitated, or ASA-PS III or IV Patients: 1 mg/kg to 1.5 mg/kg until induction onset, as determined by clinical response to the onset of anesthesia.; Cardiac Anesthesia: 0.5 mg/kg to 1.5 mg/kg until induction onset, as determined by clinical response of the patient.; Neurosurgical Patients: 1 mg/kg to 2 mg/kg until induction onset, as determined by clinical response of the patient.; Pediatric Patients – healthy, from 3 years to 16 years of age: 2.5 mg/kg to 3.5 mg/kg administered until induction onset, as determined by clinical response of the patient [see Pediatric Use (8.4) and Clinical Pharmacology (12.2)].
Maintenance of General Anesthesia: | Infusion; Healthy Adults Less Than 65 Years of Age: Infusion of 100 mcg/kg/min to 200 mcg/kg/min (6 mg/kg/hour to 12 mg/kg/hour).; Elderly, Debilitated, ASA-PS III or IV Patients: Infusion of 50 mcg/kg/min to 100 mcg/kg/min (3 mg/kg/hour to 6 mg/kg/hour).; Cardiac Anesthesia: Infusion of 25 mcg/kg/min to 100 mcg/kg/min; Neurosurgical Patients: Infusion of 100 mcg/kg/min to 200 mcg/kg/min (6 mg/kg/hour to 12 mg/kg/hour).; Pediatric Patients - healthy, from 2 months of age to 16 years of age: Infusion of 125 mcg/kg/min to 300 mcg/kg/min (7.5 mg/kg/hour to 18 mg/kg/hour). Following the first half hour of maintenance, if clinical signs of light anesthesia are not present, the infusion rate should be decreased [see Pediatric Use (8.4) and Clinical Pharmacology (12.2)]
Maintenance of General Anesthesia: | Intermittent Bolus; Healthy Adults Less Than 65 Years of Age: Increments of 20 mg to 50 mg as needed.
Initiation of MAC Sedation: | Healthy Adults Less Than 65 Years of Age: Slow infusion or slow injection techniques are recommended to avoid apnea or hypotension. Most patients require an infusion of 100 mcg/kg/min to 150 mcg/kg/min (6 mg/kg/hour to 9 mg/kg/hour) for 3 minutes to 5 minutes or a slow injection of 0.5 mg/kg over 3 minutes to 5 minutes followed immediately by a maintenance infusion.; Elderly, Debilitated, Neurosurgical, or ASA-PS III or IV Patients: Most patients require dosages similar to healthy adults. Rapid boluses are to be avoided [see Warnings and Precautions (5.12)].
Maintenance of MAC Sedation: | Healthy Adults Less Than 65 Years of Age: A variable rate infusion technique is preferable over an intermittent bolus technique. Most patients require an infusion of 25 mcg/kg/min to 75 mcg/kg/min (1.5 mg/kg/hour to 4.5 mg/kg/hour) or incremental bolus doses of 10 mg or 20 mg. In Elderly, Debilitated, Neurosurgical, or ASA-PS III or IV Patients: Most patients require 80% of the usual adult dose. A rapid (single or repeated) bolus dose should not be used [see Warnings and Precautions (5.12)].
Initiation and; Maintenance of; ICU Sedation in; Intubated,; Mechanically Ventilated; Adult Patients: | Adult Patients - Because of the residual effects of previous anesthetic or sedative agents, in most patients the initial infusion should be 5 mcg/kg/min (0.3 mg/kg/hour) for at least 5 minutes. Subsequent increments of 5 mcg/kg/min to 10 mcg/kg/min (0.3 mg/kg/hour to 0.6 mg/kg/hour) over 5 minutes to 10 minutes may be used until desired clinical effect is achieved. Maintenance rates of 5 mcg/kg/min to 50 mcg/kg/min (0.3 mg/kg/hour to 3 mg/kg/hour) or higher may be required. Administration should not exceed 4 mg/kg/hour unless the benefits outweigh the risks [see Warnings and Precautions (5.8)].; Evaluation of clinical effect and assessment of CNS function should be carried out daily throughout maintenance to determine the minimum dose of DIPRIVAN required for sedation. The tubing and any unused DIPRIVAN drug product should be discarded after 12 hours because DIPRIVAN contains no preservatives and is capable of supporting growth of microorganisms [see Dosage and Administration (2.7) and Warnings and Precautions (5.2)].

3 DOSAGE FORMS AND STRENGTHS

DIPRIVAN® (propofol) injectable emulsion, USP is available in single-dose vials as follows:

100 mg of propofol per 10 mL of an oil-in-water emulsion (10 mg per mL), 10 mL vial

200 mg of propofol per 20 mL of an oil-in-water emulsion (10 mg per mL), 20 mL vial

500 mg of propofol per 50 mL of an oil-in-water emulsion (10 mg per mL), 50 mL vial

1,000 mg of propofol per 100 mL of an oil-in-water emulsion (10 mg per mL), 100 mL vial

4 CONTRAINDICATIONS

DIPRIVAN is contraindicated in patients with a known hypersensitivity to propofol or any of DIPRIVAN components.

DIPRIVAN is contraindicated in patients with a history of anaphylaxis to eggs, egg products, soybeans or soy products.

5 WARNINGS AND PRECAUTIONS

5.1 Anaphylactic and Anaphylactoid Reactions

Use of DIPRIVAN has been associated with both fatal and life threatening anaphylactic and anaphylactoid reactions.

Clinical features of anaphylaxis, including angioedema, bronchospasm, erythema, and hypotension, occur rarely following DIPRIVAN administration.

5.2 Risks of Microbial Contamination

Strict aseptic technique must always be maintained during handling. DIPRIVAN is a single-dose parenteral product (single patient infusion vial) which contains 0.005% disodium edetate (EDTA) to inhibit the rate of growth of microorganisms, for up to 12 hours, in the event of accidental extrinsic contamination. However, DIPRIVAN can still support the growth of microorganisms, as it is not an antimicrobially preserved product under USP standards. Do not use if contamination is suspected. Discard unused drug product as directed within the required time limits. There have been reports in which failure to use aseptic technique when handling DIPRIVAN was associated with microbial contamination of the product and with fever, infection/sepsis, other life-threatening illness, and/or death.

DIPRIVAN vials are never to be accessed more than once or used on more than one person.

There have been reports, in the literature and other public sources, of the transmission of bloodborne pathogens (such as Hepatitis B, Hepatitis C, and HIV) from unsafe injection practices, and of the use of propofol vials intended for single use on multiple persons.

5.3 Risks of Pediatric Neurotoxicity

Published animal studies demonstrate that the administration of anesthetic and sedation drugs that block NMDA receptors and/or potentiate GABA activity increase neuronal apoptosis in the developing brain and result in long-term cognitive deficits when used for longer than 3 hours. The clinical significance of these findings is not clear. However, based on the available data, the window of vulnerability to these changes is believed to correlate with exposures in the third trimester of gestation through the first several months of life, but may extend out to approximately three years of age in humans [see Animal Toxicology and/or Pharmacology (13.2)].

Some published studies in children suggest that similar deficits may occur after repeated or prolonged exposures to anesthetic agents early in life and may result in adverse cognitive or behavioral effects. These studies have substantial limitations, and it is not clear if the observed effects are due to the anesthetic/sedation drug administration or other factors such as the surgery or underlying illness.

Anesthetic and sedation drugs are a necessary part of the care of children needing surgery, other procedures, or tests that cannot be delayed, and no specific medications have been shown to be safer than any other. Decisions regarding the timing of any elective procedures requiring anesthesia should take into consideration the benefits of the procedure weighed against the potential risks.

5.4 Risks of Bradycardia, Asystole, and Cardiac Arrest

DIPRIVAN has no vagolytic activity. Reports of bradycardia, asystole, and rarely, cardiac arrest have been associated with DIPRIVAN. Pediatric patients are susceptible to this effect, particularly when fentanyl is given concomitantly.

The intravenous administration of anticholinergic agents (e.g., atropine or glycopyrrolate) should be considered to modify potential increases in vagal tone due to concomitant agents (e.g., succinylcholine) or surgical stimuli.

5.5 Risk of Seizures

When DIPRIVAN is administered to an epileptic patient, there is a risk of seizure during the recovery phase.

5.6 Neurosurgical Anesthesia

When DIPRIVAN is used in patients with increased intracranial pressure or impaired cerebral circulation, significant decreases in mean arterial pressure should be avoided because of the resultant decreases in cerebral perfusion pressure. To avoid significant hypotension and decreases in cerebral perfusion pressure, an infusion or slow bolus should be utilized instead of rapid, more frequent, and/or larger boluses of DIPRIVAN. Slower induction, titrated to clinical responses, will generally result in reduced induction dosage requirements (1 mg/kg to 2 mg/kg). When increased ICP is suspected, hyperventilation and hypocarbia should accompany the administration of DIPRIVAN [see Dosage and Administration (2.1)].

5.7 Cardiac Anesthesia

Slower rates of administration should be utilized in premedicated patients, geriatric patients, patients with recent fluid shifts, and patients who are hemodynamically unstable. Fluid deficits should be corrected prior to administration of DIPRIVAN. In those patients where additional fluid therapy may be contraindicated, other measures, e.g., elevation of lower extremities, or use of pressor agents, may be useful to offset the hypotension which is associated with the induction of anesthesia with DIPRIVAN.

5.8 Use for Intensive Care Unit Sedation of Intubated, Mechanically Ventilated Adult Patients

The administration of DIPRIVAN should be initiated as a continuous infusion and changes in the rate of administration made slowly (>5 min) in order to minimize hypotension and avoid acute overdosage [see Overdosage (10) and Dosage and Administration (2.5)].

Patients should be monitored for early signs of significant hypotension and/or cardiovascular depression, which may be profound. These effects are responsive to discontinuation of DIPRIVAN, intravenous fluid administration, and/or vasopressor therapy. In the elderly, debilitated, or ASA-PS III or IV patients, rapid (single or repeated) bolus administration should not be used during sedation in order to minimize undesirable cardiorespiratory depression.

As with other sedative medications, there is wide interpatient variability in DIPRIVAN dosage requirements, and these requirements may change with time.

Failure to reduce the infusion rate in patients receiving DIPRIVAN for extended periods may result in excessively high blood concentrations of the drug. Thus, titration to clinical response and daily evaluation of sedation levels are important during use of DIPRIVAN infusion for ICU sedation, especially when it is used for long durations.

Opioids and paralytic agents should be discontinued and respiratory function optimized prior to weaning patients from mechanical ventilation. Infusions of DIPRIVAN should be adjusted to maintain a light level of sedation prior to weaning patients from mechanical ventilatory support. Throughout the weaning process, this level of sedation may be maintained in the absence of respiratory depression.

Abrupt discontinuation of DIPRIVAN prior to weaning or for daily evaluation of sedation levels should be avoided. This may result in rapid awakening with associated anxiety, agitation, and resistance to mechanical ventilation. It is therefore recommended that administration of DIPRIVAN be continued in order to maintain a light level of sedation throughout the weaning process until 10 to 15 minutes prior to extubation, at which time the infusion can be discontinued.

5.9 Risks of Propofol Infusion Syndrome in Patients with ICU Sedation

Use of DIPRIVAN infusions for both adult and pediatric ICU sedation has been associated with a constellation of metabolic derangements and organ system failures, referred to as Propofol Infusion Syndrome, that have resulted in death. The syndrome is characterized by severe metabolic acidosis, hyperkalemia, lipemia, rhabdomyolysis, hepatomegaly, renal failure, ECG changes (Coved ST segment elevation -similar to ECG changes of the Brugada syndrome) and/or cardiac failure.

The following appear to be major risk factors for the development of these events: decreased oxygen delivery to tissues; serious neurological injury and/or sepsis; high dosages of one or more of the following pharmacological agents: vasoconstrictors, steroids, inotropes and/or prolonged, high-dose infusions of propofol (> 5 mg/kg/hour for > 48 hours). The syndrome has also been reported following large-dose, short-term infusions during surgical anesthesia. In the setting of prolonged need for sedation, increasing propofol dose requirements to maintain a constant level of sedation, or onset of metabolic acidosis during administration of a propofol infusion, consideration should be given to using alternative means of sedation.

Prescribers should be alert to these events in patients with the above risk factors and immediately discontinue propofol when the above signs develop.

5.10 Risk of Elevations in Serum Triglycerides

DIPRIVAN use requires caution when administered to patients with disorders of lipid metabolism such as primary hyperlipoproteinemia, diabetic hyperlipemia, and pancreatitis.

Since DIPRIVAN is formulated in an oil-in-water emulsion, elevations in serum triglycerides may occur when DIPRIVAN is administered for extended periods of time. Patients at risk of hyperlipidemia should be monitored for increases in serum triglycerides or serum turbidity. Administration of DIPRIVAN should be adjusted if fat is being inadequately cleared from the body. A reduction in the quantity of concurrently administered lipids is indicated to compensate for the amount of lipid infused as part of the DIPRIVAN formulation; 1 mL of DIPRIVAN contains approximately 0.1 g of fat (1.1 kcal).

5.11 Risks of Zinc Losses

EDTA is a strong chelator of trace metals – including zinc. Although with DIPRIVAN there are no reports of decreased zinc levels or zinc deficiency-related adverse events, DIPRIVAN should not be infused for longer than 5 days without providing a drug holiday to safely replace estimated or measured urine zinc losses.

In clinical trials mean urinary zinc loss was approximately 2.5 mg/day to 3 mg/day in adult patients and 1.5 mg/day to 2 mg/day in pediatric patients.

In patients who are predisposed to zinc deficiency, such as those with burns, diarrhea, and/or major sepsis, the need for supplemental zinc should be considered during prolonged therapy with DIPRIVAN.

5.12 Use in the Elderly, Debilitated, or ASA-PS III or IV Patients

A lower induction dose and a slower maintenance rate of administration should be used in elderly, debilitated, or ASA-PS III or IV patients [see Dosage and Administration (2)]. Patients should be continuously monitored for early signs of hypotension and/or bradycardia. Apnea requiring ventilatory support often occurs during induction and may persist for more than 60 seconds.

5.13 Risk of Transient Local Pain

Attention should be paid to minimize pain on administration of DIPRIVAN. Transient local pain can be minimized if the larger veins of the forearm or antecubital fossa are used. Pain during intravenous injection may also be reduced by prior injection of intravenous lidocaine (1 mL of a 1% solution). Pain on injection occurred frequently in pediatric patients (45%) when a small vein of the hand was utilized without lidocaine pretreatment. With lidocaine pretreatment or when antecubital veins were utilized, pain was minimal (incidence less than 10%) and well-tolerated.

There have been reports in the literature indicating that the addition of lidocaine to DIPRIVAN in quantities greater than 20 mg lidocaine/200 mg DIPRIVAN results in instability of the emulsion which is associated with increases in globule sizes over time and (in rat studies) a reduction in anesthetic potency. Therefore, it is recommended that lidocaine be administered prior to DIPRIVAN administration or that it be added to DIPRIVAN immediately before administration and in quantities not exceeding 20 mg lidocaine/200 mg DIPRIVAN.

5.14 Risks of Local Reactions

Phlebitis or venous thrombosis has been reported. In two clinical studies using dedicated intravenous catheters, no instances of venous sequelae were observed up to 14 days following induction.

Accidental intra-arterial injection has been reported in patients, and, other than pain, there were no major sequelae.

5.15 Risks of Aggregation if Administered through the Same Intravenous Catheter with Blood or Plasma

DIPRIVAN should not be coadministered through the same intravenous catheter with blood or plasma because compatibility has not been established. In vitro tests have shown that aggregates of the globular component of the emulsion vehicle have occurred with blood/plasma/serum from humans and animals. The clinical significance of these findings is not known.

5.16 Risk of Postoperative Unconsciousness

Very rarely the use of DIPRIVAN may be associated with the development of a period of postoperative unconsciousness which may be accompanied by an increase in muscle tone. This may or may not be preceded by a brief period of wakefulness. Recovery is spontaneous.

5.17 Risks of Perioperative Myoclonia

Perioperative myoclonia, rarely including convulsions and opisthotonos, has occurred in association with DIPRIVAN administration.

5.18 Risks of Pulmonary Edema

There have been rare reports of pulmonary edema in temporal relationship to the administration of DIPRIVAN, although a causal relationship is unknown.

5.19 Risks of Unexplained Postoperative Pancreatitis

Rarely, cases of unexplained postoperative pancreatitis (requiring hospital admission) have been reported after anesthesia in which DIPRIVAN was one of the induction agents used. Due to a variety of confounding factors in these cases, including concomitant medications, a causal relationship to DIPRIVAN is unclear.

6 ADVERSE REACTIONS

The following serious or otherwise important adverse reactions are discussed elsewhere in the labeling:

- Hypersensitivity reaction [see Warnings and Precautions (5.1)]
- Hypotension and/or bradycardia [see Warnings and Precautions (5.4)]
- Propofol Infusion Syndrome [see Warnings and Precautions (5.9)]

In the description below, rates of the more common events represent US/Canadian clinical study results. Less frequent events are also derived from publications and marketing experience in over 8 million patients; there are insufficient data to support an accurate estimate of their incidence rates. These studies were conducted using a variety of premedicants, varying lengths of surgical/diagnostic procedures, and various other anesthetic/sedative agents. Most adverse events were mild and transient.

Clinical Trials Experience

Because clinical trials are conducted under widely varying conditions, adverse reaction rates observed in the clinical trials of a drug cannot be directly compared to rates in the clinical trials of another drug and may not reflect the rates observed in practice.

Anesthesia and MAC Sedation in Adults

The following estimates of adverse events for DIPRIVAN include data from clinical trials in general anesthesia/MAC sedation (N=2889 adult patients). The adverse events listed below as probably causally related are those events in which the actual incidence rate in patients treated with DIPRIVAN was greater than the comparator incidence rate in these trials. Therefore, incidence rates for anesthesia and MAC sedation in adults generally represent estimates of the percentage of clinical trial patients which appeared to have probable causal relationship.

The adverse experience profile from reports of 150 patients in the MAC sedation clinical trials is similar to the profile established with DIPRIVAN during anesthesia (see Table 3 below). During MAC sedation clinical trials, significant respiratory events included cough, upper airway obstruction, apnea, hypoventilation, and dyspnea.

Anesthesia in Pediatric Patients

Generally, the adverse experience profile from reports of 506 DIPRIVAN pediatric patients from 6 days through 16 years of age in the US/Canadian anesthesia clinical trials is similar to the profile established with DIPRIVAN during anesthesia in adults. Although not reported as an adverse event in clinical trials, apnea is frequently observed in pediatric patients.

ICU Sedation in Adults

The following estimates of adverse events include data from clinical trials in ICU sedation (N=159 adult patients). Probably related incidence rates for ICU sedation were determined by individual case report form review. Probable causality was based upon an apparent dose response relationship and/or positive responses to rechallenge. In many instances the presence of concomitant disease and concomitant therapy made the causal relationship unknown. Therefore, incidence rates for ICU sedation generally represent estimates of the percentage of clinical trial patients which appeared to have a probable causal relationship.

Table 2. Treatment Emergent Adverse Events Observed from Clinical Trials
 | Anesthesia/MAC Sedation | ICU Sedation
Body as a Whole: | Anaphylaxis/Anaphylactoid reaction perinatal disorder, tachycardia , bigeminy, bradycardia, premature ventricular contractions , hemorrhage, ECG abnormal arrhythmia atrial, fever, extremities pain , anticholinergic syndrome, asthenia, awareness, chest pain, extremities pain, fever, increased drug effect, neck rigidity/stiffness, trunk pain | Fever, sepsis, trunk pain, whole body weakness
Cardiovascular: | Premature atrial contractions Syncope, hypotension [see also Clinical Pharmacology (12)], tachycardia Nodal, arrhythmia Bradycardia, arrhythmia, atrial fibrillation, atrioventricular heart block, bigeminy, bleeding, bundle branch block, cardiac arrest, ECG abnormal, edema, extrasystole, heart block, hypertension, myocardial infarction, myocardial ischemia, premature ventricular contractions, ST segment depression, supraventricular tachycardia, tachycardia, ventricular fibrillation | Bradycardia, decreased cardiac output, arrhythmia, atrial fibrillation, bigeminy, cardiac arrest, extrasystole, right heart failure, ventricular tachycardia
Central Nervous System: | Hypertonia/Dystonia, paresthesia, movement, abnormal dreams, agitation, amorous behavior, anxiety, bucking/jerking/thrashing, chills/shivering/clonic/myoclonic movement, combativeness, confusion, delirium, depression, dizziness, emotional lability, euphoria, fatigue, hallucinations, headache, hypotonia, hysteria, insomnia, moaning, neuropathy, opisthotonos, rigidity, seizures, somnolence, tremor, twitching | Agitation, hypotension, hills/shivering, intracranial hypertension, seizures, somnolence, thinking abnormal
Digestive: | Hypersalivation, nausea, cramping, diarrhea, dry mouth, enlarged parotid, nausea, swallowing, vomiting | Ileus, liver function abnormal
Hemic/Lymphatic: | Leukocytosis, coagulation disorder, leukocytosis
Injection Site: | Phlebitis, pruritus, burning/Stinging or pain, hives/itching, phlebitis, redness/discoloration
Metabolic/Nutritional: | hypomagnesemia, hyperkalemia, hyperlipemia | BUN increased, creatinine increased, dehydration, hyperglycemia, metabolic acidosis, osmolality increased, hyperlipemia
Musculoskeletal: | Myalgia
Nervous: | Dizziness, agitation, chills, somnolence Delirium
Respiratory: | Wheezing, cough, laryngospasm, hypoxia, apnea, bronchospasm, burning in throat, dyspnea, hiccough, hyperventilation, hypoventilation, pharyngitis, sneezing, tachypnea, upper airway obstruction | Decreased lung function, respiratory acidosis during weaning, hypoxia
Skin and Appendages: | Flushing, Pruritus, rash, conjunctival hyperemia, diaphoresis, urticaria | Rash
Special Senses: | Amblyopia, vision abnormal, diplopia, ear pain, eye pain, nystagmus, taste perversion, tinnitus
Urogenital: | Cloudy urine, oliguria, urine retention | Green urine, kidney failure

Postmarketing Experience

During the post-marketing period, there have been rare reports of local pain, swelling, blisters, and/or tissue necrosis following accidental extravasation of DIPRIVAN [see Warnings and Precautions (5.14)].

Venous sequelae, i.e., phlebitis or thrombosis, have been reported rarely (<1%).

7 DRUG INTERACTIONS

Opioids and Sedatives

The induction dose requirements of DIPRIVAN may be reduced in patients with intramuscular or intravenous premedication, particularly with opioids (e.g., morphine, meperidine, and fentanyl, etc.) and combinations of opioids and sedatives (e.g., benzodiazepines, barbiturates, chloral hydrate, droperidol, etc.). These agents may increase the anesthetic or sedative effects of DIPRIVAN and may also result in more pronounced decreases in systolic, diastolic, and mean arterial pressures and cardiac output.

In pediatric patients, administration of fentanyl concomitantly with DIPRIVAN may result in serious bradycardia.

Analgesic Agents

During maintenance of anesthesia or sedation, the rate of DIPRIVAN administration should be adjusted according to the desired level of anesthesia or sedation and may be reduced in the presence of supplemental analgesic agents (e.g., nitrous oxide or opioids).

The concurrent administration of potent inhalational agents (e.g., isoflurane, sevoflurane, desflurane, enflurane, and halothane) during maintenance with DIPRIVAN are routinely used. These inhalational agents can also be expected to increase the anesthetic or sedative and cardiorespiratory effects of DIPRIVAN.

Valproate

The concomitant use of valproate and propofol may lead to increased blood levels of propofol. Reduce the dose of propofol when co-administering with valproate. Monitor patients closely for signs of increased sedation or cardiorespiratory depression.

Common Neuromuscular Blocking Agents

DIPRIVAN does not cause a clinically significant change in onset, intensity or duration of action of the commonly used neuromuscular blocking agents (e.g., succinylcholine and nondepolarizing muscle relaxants).

Common Drugs Used as Premedication or Drugs Used During Anesthesia or Sedation

No significant adverse interactions with commonly used premedications or drugs used during anesthesia or sedation (including a range of muscle relaxants, inhalational agents, analgesic agents, and local anesthetic agents) have been observed in adults.

8 USE IN SPECIFIC POPULATIONS

8.1 Pregnancy

Risk Summary

Data from randomized controlled trials, cohort studies and case series over several decades with propofol use in pregnant women have not identified a drug-associated risk of major birth defects, miscarriage, or adverse maternal or fetal outcomes. Most of the reported exposures to propofol describe propofol exposure at the time of cesarean delivery. There are reports of neonatal depression in infants exposed to propofol during delivery (see Clinical Considerations). In animal reproduction studies, decreased pup survival concurrent with increased maternal mortality was observed with intravenous administration of propofol to pregnant rats either prior to mating and during early gestation or during late gestation and early lactation at exposures less than the human induction dose of 2.5 mg/kg. In pregnant rats administered 15 mg/kg/day intravenous propofol (equivalent to the human induction dose) from two weeks prior to mating to early in gestation (Gestation Day 7), offspring that were allowed to mate had increased postimplantation losses. The pharmacological activity (anesthesia) of the drug on the mother is probably responsible for the adverse effects seen in the offspring.

Published studies in pregnant primates demonstrate that the administration of anesthetic and sedation drugs that block NMDA receptors and/or potentiate GABA activity during the period of peak brain development increases neuronal apoptosis in the developing brain of the offspring when used for longer than 3 hours. There are no data on pregnancy exposures in primates corresponding to periods prior to the third trimester in humans [see Data, Warnings and Precautions (5.3), Use in Specific Populations (8.4)]). The clinical significance of these nonclinical findings is not known, and the benefits of appropriate anesthesia in pregnant women who require procedures should be balanced with the potential risks suggested by the nonclinical data.

The estimated background risk of major birth defects and miscarriage for the indicated population is unknown. All pregnancies have a background risk of birth defect, loss, or other adverse outcomes. In the U.S. general population, the estimated background risk of major birth defects and miscarriage in clinically recognized pregnancies is 2–4% and 15–20%, respectively.

Clinical Considerations

Fetal/neonatal Adverse Reactions

DIPRIVAN crosses the placenta and may be associated with neonatal depression. Monitor neonates for hypotonia and sedation following maternal exposure to propofol.

Data

Animal Data

Pregnant rats were administered propofol intravenously at 0, 5, 10, and 15 mg/kg/day (0.3, 0.65, and 1 times the human induction dose of 2.5 mg/kg based on body surface area) during organogenesis (Gestational Days 6–15). Propofol did not cause adverse effects to the fetus at exposures up to 1 times the human induction dose despite evidence of maternal toxicity (decreased weight gain in all groups).

Pregnant rabbits were administered propofol intravenously at 0, 5, 10, and 15 mg/kg/day (0.65, 1.3, 2 times the human induction dose of 2.5 mg/kg based on body surface area comparison) during organogenesis (Gestation Days 6–18). Propofol treatment decreased total numbers of corpora lutea in all treatment groups but did not cause fetal malformations at any dose despite maternal toxicity (one maternal death from anesthesia-related respiratory depression in the high dose group).

Pregnant rats were administered propofol intravenously at 0, 10, and 15 mg/kg/day (0.65 and 1 times the human induction dose of 2.5 mg/kg based on body surface area) from late gestation through lactation (Gestation Day 16 to Lactation Day 22). Decreased pup survival was noted at all doses in the presence of maternal toxicity (deaths from anesthesia- induced respiratory depression). This study did not evaluate neurobehavioral function including learning and memory in the pups.

Pregnant rats were administered propofol intravenously at 0, 10, or 15 mg/kg/day (0.3 and 1 times the human induction dose of 2.5 mg/kg based on body surface area) from 2 weeks prior to mating to Gestational Day 7. Pup (F1) survival was decreased on Day 15 and 22 of lactation at maternally toxic doses of 10 and 15 mg/kg/day. When F1 offspring were allowed to mate, postimplantation losses were increased in the 15 mg/kg/day treatment group.

In a published study in primates, administration of an anesthetic dose of ketamine for 24 hours on Gestation Day 122 increased neuronal apoptosis in the developing brain of the fetus. In other published studies, administration of either isoflurane or propofol for 5 hours on Gestation Day 120 resulted in increased neuronal and oligodendrocyte apoptosis in the developing brain of the offspring. With respect to brain development, this time period corresponds to the third trimester of gestation in the human. The clinical significance of these findings is not clear; however, studies in juvenile animals suggest neuroapoptosis correlates with long-term cognitive deficits [see Warnings and Precautions (5.3), Pediatric Use (8.4), and Animal Toxicology and/or Pharmacology (13.2)].

8.2 Lactation

Risk Summary

Based on data from published studies, propofol is present in human milk. Variable concentrations have been reported in human milk with administration of propofol to nursing mothers in the early post-partum period. Available data have not shown adverse reactions in breastfed infants. There are no data on the effects of propofol on milk production. The developmental and health benefits of breastfeeding should be considered along with the mother’s clinical need for DIPRIVAN and any potential adverse effects on the breastfed infant form DIPRIVAN or from the underlying maternal condition.

8.4 Pediatric Use

The safety and effectiveness of DIPRIVAN have been established for induction of anesthesia in pediatric patients aged 3 years and older and for the maintenance of anesthesia aged 2 months and older.

In pediatric patients, administration of fentanyl concomitantly with DIPRIVAN may result in serious bradycardia [see Warnings and Precautions (5.4)].

DIPRIVAN is not indicated for use in pediatric patients for ICU sedation or for MAC sedation for surgical, nonsurgical or diagnostic procedures as safety and effectiveness have not been established.

There have been anecdotal reports of serious adverse events and death in pediatric patients with upper respiratory tract infections receiving DIPRIVAN for ICU sedation.

In one multicenter clinical trial of ICU sedation in critically ill pediatric patients that excluded patients with upper respiratory tract infections, the incidence of mortality observed in patients who received DIPRIVAN (n=222) was 9%, while that for patients who received standard sedative agents (n=105) was 4%. While causality was not established in this study, DIPRIVAN is not indicated for ICU sedation in pediatric patients until further studies have been performed to document its safety in that population [see Clinical Pharmacology (12.3) and Dosage and Administration (2.1 and 2.2)]. However, propofol infusions are routinely used to provide safe sedation to critically ill pediatric patients in ICUs.

In pediatric patients, abrupt discontinuation of DIPRIVAN following prolonged infusion may result in flushing of the hands and feet, agitation, tremulousness and hyperirritability. Increased incidences of bradycardia (5%), agitation (4%), and jitteriness (9%) have also been observed.

Published juvenile animal studies demonstrate that the administration of anesthetic and sedation drugs, such as DIPRIVAN, that either block NMDA receptors or potentiate the activity of GABA during the period of rapid brain growth or synaptogenesis, results in widespread neuronal and oligodendrocyte cell loss in the developing brain and alterations in synaptic morphology and neurogenesis. Based on comparisons across species, the window of vulnerability to these changes is believed to correlate with exposures in the third trimester of gestation through the first several months of life, but may extend out to approximately 3 years of age in humans.

In primates, exposure to 3 hours of ketamine that produced a light surgical plane of anesthesia did not increase neuronal cell loss, however, treatment regimens of 5 hours or longer of isoflurane increased neuronal cell loss. Data from isoflurane-treated rodents and ketamine-treated primates suggest that the neuronal and oligodendrocyte cell losses are associated with prolonged cognitive deficits in learning and memory. The clinical significance of these nonclinical findings is not known, and healthcare providers should balance the benefits of appropriate anesthesia in pregnant women, neonates, and young children who require procedures with the potential risks suggested by the nonclinical data [see Warnings and Precaution (5.3), Pregnancy (8.1), and Animal Toxicology and/or Pharmacology (13.2)].

8.5 Geriatric Use

The effect of age on induction dose requirements for propofol was assessed in an open-label study involving 211 unpremedicated patients with approximately 30 patients in each decade between the ages of 16 and 80. The average dose to induce anesthesia was calculated for patients up to 54 years of age and for patients 55 years of age or older. The average dose to induce anesthesia in patients up to 54 years of age was 1.99 mg/kg and in patients above 54 it was 1.66 mg/kg. Subsequent clinical studies have demonstrated lower dosing requirements for subjects greater than 60 years of age.

A lower induction dose and a slower maintenance rate of administration of DIPRIVAN should be used in elderly patients. In this group of patients, rapid (single or repeated) bolus administration should not be used in order to minimize undesirable cardiorespiratory depression. All dosing should be titrated according to patient condition and response [see Dosage and Administration (2) and Clinical Pharmacology (12.3)].

8.6 Hepatic Impairment

The long-term administration of DIPRIVAN to patients with hepatic insufficiency has not been evaluated.

The pharmacokinetics of propofol do not appear to be different in people with chronic hepatic cirrhosis compared to adults with normal hepatic function. The effects of acute hepatic failure on the pharmacokinetics of propofol have not been studied.

8.7 Renal Impairment

Studies to date in patients with normal or impaired renal function have not shown any alteration in renal function with DIPRIVAN containing 0.005% disodium edetate. In patients at risk for renal impairment, urinalysis and urine sediment should be checked before initiation of sedation and then be monitored on alternate days during sedation.

DIPRIVAN contains 0.005% disodium edetate. At high doses (2 to 3 grams per day), EDTA has been reported, on rare occasions, to be toxic to the renal tubules.

The long-term administration of DIPRIVAN to patients with renal failure has not been evaluated.

The pharmacokinetics of propofol do not appear to be different in people with chronic renal impairment compared to adults with normal renal function. The effects of acute renal failure on the pharmacokinetics of propofol have not been studied.

9 DRUG ABUSE AND DEPENDENCE

9.2 Abuse

There are reports of the abuse of propofol for recreational and other improper purposes, which have resulted in fatalities and other injuries. Instances of self-administration of DIPRIVAN by health care professionals have also been reported, which have resulted in fatalities and other injuries. Inventories of DIPRIVAN should be stored and managed to prevent the risk of diversion, including restriction of access and accounting procedures as appropriate to the clinical setting.

10 OVERDOSAGE

10.1 Symptoms

Overdosage is likely to cause cardiorespiratory depression.

10.2 Treatment

If overdosage occurs, DIPRIVAN administration should be discontinued immediately.

Respiratory depression should be treated by artificial ventilation with oxygen. Cardiovascular depression may require repositioning of the patient by raising the patient's legs, increasing the flow rate of intravenous fluids, and administering pressor agents and/or anticholinergic agents.

11 DESCRIPTION

DIPRIVAN® (propofol) injectable emulsion, USP is an anesthetic available as a sterile, nonpyrogenic white or almost white homogeneous emulsion for intravenous administration. The structural formula is:

Chemical name: 2,6 diisopropylphenol

Molecular formula: C12H18O

Molecular weight: 178.27

Propofol is slightly soluble in water. The pKa is 11. The octanol/water partition coefficient for propofol is 6761:1 at a pH of 6 to 8.5.

Each mL of DIPRIVAN® (Propofol) injectable emulsion, USP contains 10 mg of propofol, 100 mg of soybean oil (100 mg/mL), 22.5 mg of glycerol (22.5 mg/mL), 12 mg of purified egg phospholipids (12 mg/mL), 0.055 mg of disodium edetate anhydrous (equivalent to 0.055 mg of disodium edetate) (0.05 mg/mL) as microbial inhibitor, and sodium hydroxide to adjust pH, in water for injection. DIPRIVAN is isotonic and has a pH of 7 to 8.5.

12 CLINICAL PHARMACOLOGY

DIPRIVAN is an intravenous general anesthetic and sedation drug for use in the induction and maintenance of anesthesia or sedation. Intravenous injection of a therapeutic dose of propofol induces anesthesia, with minimal excitation, usually within 40 seconds from the start of injection (the time for one arm-brain circulation). As with other rapidly acting intravenous anesthetic agents, the half-time of the blood-brain equilibration is approximately 1 to 3 minutes, accounting for the rate of induction of anesthesia.

12.1 Mechanism of Action

The mechanism of action, like all general anesthetics, is poorly understood. However, propofol is thought to produce its sedative/anesthetic effects by the positive modulation of the inhibitory function of the neurotransmitter GABA through the ligand-gated GABAA receptors.

12.2 Pharmacodynamics

Pharmacodynamic properties of propofol are dependent upon the therapeutic blood propofol concentrations. Steady-state propofol blood concentrations are generally proportional to infusion rates. Undesirable side effects, such as cardiorespiratory depression, are likely to occur at higher blood concentrations which result from bolus dosing or rapid increases in infusion rates. An adequate interval (3 to 5 minutes) must be allowed between dose adjustments in order to assess clinical effects.

The hemodynamic effects of DIPRIVAN during induction of anesthesia vary. If spontaneous ventilation is maintained, the major cardiovascular effect is arterial hypotension (sometimes greater than a 30% decrease) with little or no change in heart rate and no appreciable decrease in cardiac output. If ventilation is assisted or controlled (positive pressure ventilation), there is an increase in the incidence and the degree of depression of cardiac output. Addition of an opioid, used as a premedicant, further decreases cardiac output and respiratory drive.

If anesthesia is continued by infusion of DIPRIVAN, the stimulation of endotracheal intubation and surgery may return arterial pressure towards normal. However, cardiac output may remain depressed. Comparative clinical studies have shown that the hemodynamic effects of DIPRIVAN during induction of anesthesia are generally more pronounced than with other intravenous induction agents.

Induction of anesthesia with DIPRIVAN is frequently associated with apnea in both adults and pediatric patients. In adult patients who received DIPRIVAN (2 mg/kg to 2.5 mg/kg), apnea lasted less than 30 seconds in 7% of patients, 30 seconds to 60 seconds in 24% of patients, and more than 60 seconds in 12% of patients. In pediatric patients from birth through 16 years of age assessable for apnea who received bolus doses of DIPRIVAN (1 mg/kg to 3.6 mg/kg), apnea lasted less than 30 seconds in 12% of patients, 30 seconds to 60 seconds in 10% of patients, and more than 60 seconds in 5% of patients.

During maintenance of general anesthesia, DIPRIVAN causes a decrease in spontaneous minute ventilation usually associated with an increase in carbon dioxide tension which may be marked depending upon the rate of administration and concurrent use of other medications (e.g., opioids, sedatives, etc.).

During monitored anesthesia care (MAC) sedation, attention must be given to the cardiorespiratory effects of DIPRIVAN. Hypotension, oxyhemoglobin desaturation, apnea, and airway obstruction can occur, especially following a rapid bolus of DIPRIVAN. During initiation of MAC sedation, slow infusion or slow injection techniques are preferable over rapid bolus administration. During maintenance of MAC sedation, a variable rate infusion is preferable over intermittent bolus administration in order to minimize undesirable cardiorespiratory effects. In the elderly, debilitated, or ASA-PS III or IV patients, rapid (single or repeated) bolus dose administration should not be used for MAC sedation [see Warnings and Precautions (5.12)].

Clinical and preclinical studies suggest that DIPRIVAN is rarely associated with elevation of plasma histamine levels.

Preliminary findings in patients with normal intraocular pressure indicate that DIPRIVAN produces a decrease in intraocular pressure which may be associated with a concomitant decrease in systemic vascular resistance.

Clinical studies indicate that DIPRIVAN when used in combination with hypocarbia increases cerebrovascular resistance and decreases cerebral blood flow, cerebral metabolic oxygen consumption, and intracranial pressure. DIPRIVAN does not affect cerebrovascular reactivity to changes in arterial carbon dioxide tension [see Clinical Studies (14.2)].

Clinical studies indicate that DIPRIVAN does not suppress the adrenal response to ACTH.

Animal studies and limited experience in susceptible patients have not indicated any propensity of DIPRIVAN to induce malignant hyperthermia.

Hemosiderin deposits have been observed in the livers of dogs receiving DIPRIVAN containing 0.005% disodium edetate over a four-week period; the clinical significance of this is unknown.

12.3 Pharmacokinetics

The pharmacokinetics of propofol are well described by a three- compartment linear model with compartments representing the plasma, rapidly equilibrating tissues, and slowly equilibrating tissues.

Following an intravenous bolus dose, there is rapid equilibration between the plasma and the brain, accounting for the rapid onset of anesthesia. Plasma levels initially decline rapidly as a result of both distribution and metabolic clearance. Distribution accounts for about half of this decline following a bolus of propofol. However, distribution is not constant over time, but decreases as body tissues equilibrate with plasma and become saturated. The rate at which equilibration occurs is a function of the rate and duration of the infusion. When equilibration occurs there is no longer a net transfer of propofol between tissues and plasma.

Discontinuation of the recommended doses of DIPRIVAN after the maintenance of anesthesia for approximately one hour, or for sedation in the ICU for one day, results in a prompt decrease in blood propofol concentrations and rapid awakening. Longer infusions (10 days of ICU sedation) result in accumulation of significant tissue stores of propofol, such that the reduction in circulating propofol is slowed and the time to awakening is increased.

By daily titration of DIPRIVAN dosage to achieve only the minimum effective therapeutic concentration, rapid awakening within 10 to 15 minutes can occur even after long-term administration. If, however, higher than necessary infusion levels have been maintained for a long time, propofol redistribution from fat and muscle to the plasma can be significant and slow recovery.

The figure below illustrates the fall of plasma propofol levels following infusions of various durations to provide ICU sedation.

The large contribution of distribution (about 50%) to the fall of propofol plasma levels following brief infusions means that after very long infusions a reduction in the infusion rate is appropriate by as much as half the initial infusion rate in order to maintain a constant plasma level. Therefore, failure to reduce the infusion rate in patients receiving DIPRIVAN for extended periods may result in excessively high blood concentrations of the drug. Thus, titration to clinical response and daily evaluation of sedation levels are important during use of DIPRIVAN infusion for ICU sedation.

Adults

Propofol clearance ranges from 23 mL/kg/min to 50 mL/kg/min (1.6 L/min to 3.4 L/min in 70 kg adults). It is chiefly eliminated by hepatic conjugation to inactive metabolites which are excreted by the kidney. A glucuronide conjugate accounts for about 50% of the administered dose. Propofol has a steady-state volume of distribution (10-day infusion) approaching 60 L/kg in healthy adults. A difference in pharmacokinetics due to gender has not been observed. The terminal half-life of propofol after a 10-day infusion is 1 day to 3 days.

Geriatrics

With increasing patient age, the dose of propofol needed to achieve a defined anesthetic end point (dose-requirement) decreases. This does not appear to be an age-related change in pharmacodynamics or brain sensitivity, as measured by EEG burst suppression. With increasing patient age, pharmacokinetic changes are such that, for a given intravenous bolus dose, higher peak plasma concentrations occur, which can explain the decreased dose requirement. These higher peak plasma concentrations in the elderly can predispose patients to cardiorespiratory effects including hypotension, apnea, airway obstruction, and/or arterial oxygen desaturation. The higher plasma levels reflect an age-related decrease in volume of distribution and intercompartmental clearance. Lower doses are therefore recommended for initiation and maintenance of sedation and anesthesia in elderly patients [see Dosage and Administration (2)].

Pediatrics

The pharmacokinetics of propofol were studied in children between 3 years and 12 years of age who received DIPRIVAN for periods of approximately 1 to 2 hours. The observed distribution and clearance of propofol in these children were similar to adults.

Organ Failure

The pharmacokinetics of propofol do not appear to be different in people with chronic hepatic cirrhosis or chronic renal impairment compared to adults with normal hepatic and renal function. The effects of acute hepatic or renal failure on the pharmacokinetics of propofol have not been studied [see Specific Populations (8.6) and (8.7)].

13 NONCLINICAL TOXICOLOGY

13.1 Carcinogenesis, Mutagenesis, Impairment of Fertility

Carcinogenesis

Long-term studies in animals have not been performed to evaluate the carcinogenic potential of propofol.

Mutagenesis

Propofol was not mutagenic in the in vitro bacterial reverse mutation assay (Ames test) using Salmonella typhimurium strains TA98, TA100, TA1535, TA1537 and TA1538. Propofol was not mutagenic in either the gene mutation/gene conversion test using Saccharomyces cerevisiae, or in vitro cytogenetic studies in Chinese hamsters. In the in vivo mouse micronucleus assay with Chinese Hamsters propofol administration did not produce chromosome aberrations.

Impairment of Fertility

Female Wistar rats were administered either 0, 10, or 15 mg/kg/day propofol intravenously from 2 weeks before pregnancy to day 7 of gestation did not show impaired fertility (0.65 and 1 times the human induction dose of 2.5 mg/kg based on body surface area). Male fertility in rats was not affected in a dominant lethal study at intravenous doses up to 15 mg/kg/day for 5 days.

13.2 Animal Toxicology and/or Pharmacology

Intra-arterial injection in animals did not induce local tissue effects. Intentional injection into subcutaneous or perivascular tissues of animals caused minimal tissue reaction.

Published studies in animals demonstrate that the use of anesthetic agents during the period of rapid brain growth or synaptogenesis results in widespread neuronal and oligodendrocyte cell loss in the developing brain and alterations in synaptic morphology and neurogenesis. Based on comparisons across species, the window of vulnerability to these changes is believed to correlate with exposures in the third trimester through the first several months of life, but may extend out to approximately 3 years of age in humans.

In primates, exposure to 3 hours of an anesthetic regimen that produced a light surgical plane of anesthesia did not increase neuronal cell loss, however, treatment regimens of 5 hours or longer increased neuronal cell loss. Data in rodents and in primates suggest that the neuronal and oligodendrocyte cell losses are associated with subtle but prolonged cognitive deficits in learning and memory. The clinical significance of these nonclinical findings is not known, and healthcare providers should balance the benefits of appropriate anesthesia in neonates and young children who require procedures against the potential risks suggested by the nonclinical data [see Warnings and Precautions (5.3); Pregnancy (8.1), and Pediatric Use (8.4)].

14 CLINICAL STUDIES

14.1 Pediatric Anesthesia

DIPRIVAN was studied in clinical trials which included cardiac surgical patients. Most patients were 3 years of age or older. The majority of the patients were healthy ASA-PS I or II patients. The range of doses in these studies are described in Tables 3 and 4.

Table 3. Pediatric Induction of Anesthesia
Age Range | Induction Dose Median (range) | Injection Duration Median (range)
≥ 3 years to 16 years | 2.5 mg/kg (1 mg/kg to 3.6 mg/kg) | 20 sec (6 sec to 45 sec)

Table 4. Pediatric Maintenance of Anesthesia
Age Range | Maintenance Dosage (mcg/kg/min) | Duration (minutes)
2 months to 2 years | 199 (82 to 394) | 65 (12 to 282)
2 to 12 years | 188 (12 to 1041) | 69 (23 to 374)
>12 through 16 years | 161 (84 to 359) | 69 (26 to 251)

14.2 Neuroanesthesia

DIPRIVAN was studied in patients undergoing craniotomy for supratentorial tumors in two clinical trials. The mean lesion size (anterior/posterior × lateral) was 31 mm × 32 mm in one trial and 55 mm × 42 mm in the other trial respectively. Anesthesia was induced with a median DIPRIVAN dose of 1.4 mg/kg (range: 0.9 mg/kg to 6.9 mg/kg) and maintained with a median maintenance DIPRIVAN dose of 146 mcg/kg/min (range: 68 mcg/kg/min to 425 mcg/kg/min). The median duration of the DIPRIVAN maintenance infusion was 285 minutes (range: 48 minutes to 622 minutes).

DIPRIVAN was administered by infusion in a controlled clinical trial to evaluate its effect on cerebrospinal fluid pressure (CSFP). The mean arterial pressure was maintained relatively constant over 25 minutes with a change from baseline of -4% ± 17% (mean ± SD). The change in CSFP was -46% ± 14%. As CSFP is an indirect measure of intracranial pressure (ICP), DIPRIVAN, when given by infusion or slow bolus in combination with hypocarbia, is capable of decreasing ICP independent of changes in arterial pressure.

14.3 Cardiac Anesthesia

DIPRIVAN was evaluated in clinical trials involving patients undergoing coronary artery bypass graft (CABG).

In post-CABG (coronary artery bypass graft) patients, the maintenance rate of propofol administration was usually low (median 11 mcg/kg/min) due to the intraoperative administration of high opioid doses. Patients receiving DIPRIVAN required 35% less nitroprusside than midazolam patients. During initiation of sedation in post-CABG patients, a 15% to 20% decrease in blood pressure was seen in the first 60 minutes. It was not possible to determine cardiovascular effects in patients with severely compromised ventricular function.

14.4 Intensive Care Unit (ICU) Sedation in Adult Patients

DIPRIVAN was compared to benzodiazepines and opioids in clinical trials involving ICU patients. Of these, 302 received DIPRIVAN and comprise the overall safety database for ICU sedation.

Across all clinical studies, the mean infusion maintenance rate for all DIPRIVAN patients was 27 ± 21 mcg/kg/min. The maintenance infusion rates required to maintain adequate sedation ranged from 2.8 mcg/kg/min to 130 mcg/kg/min. The infusion rate was lower in patients over 55 years of age (approximately 20 mcg/kg/min) compared to patients under 55 years of age (approximately 38 mcg/kg/min). Although there are reports of reduced analgesic requirements, most patients received opioids for analgesia during maintenance of ICU sedation. In these studies, morphine or fentanyl was used as needed for analgesia. Some patients also received benzodiazepines and/or neuromuscular blocking agents. During long-term maintenance of sedation, some ICU patients were awakened once or twice every 24 hours for assessment of neurologic or respiratory function.

In Medical and Postsurgical ICU studies comparing DIPRIVAN to benzodiazepine infusion or bolus, there were no apparent differences in maintenance of adequate sedation, mean arterial pressure, or laboratory findings. Like the comparators, DIPRIVAN reduced blood cortisol during sedation while maintaining responsivity to challenges with adrenocorticotropic hormone (ACTH). Case reports from the published literature generally reflect that DIPRIVAN has been used safely in patients with a history of porphyria or malignant hyperthermia.

In hemodynamically stable head trauma patients ranging in age from 19 to 43 years, adequate sedation was maintained with DIPRIVAN or morphine. There were no apparent differences in adequacy of sedation, intracranial pressure, cerebral perfusion pressure, or neurologic recovery between the treatment groups. In literature reports of severely head injured patients in Neurosurgical ICUs, DIPRIVAN infusion and hyperventilation, both with and without diuretics, controlled intracranial pressure while maintaining cerebral perfusion pressure. In some patients, bolus doses resulted in decreased blood pressure and compromised cerebral perfusion pressure.

DIPRIVAN was found to be effective in status epilepticus which was refractory to the standard anticonvulsant therapies. For these patients, as well as for ARDS/respiratory failure and tetanus patients, sedation maintenance dosages were generally higher than those for other critically ill patient populations.

14.5 Intensive Care Unit (ICU) Sedation in Pediatric Patients

A single, randomized, controlled, clinical trial that evaluated the safety and effectiveness of DIPRIVAN versus standard sedative agents (SSA) was conducted on 327 pediatric ICU patients. Patients were randomized to receive either DIPRIVAN 2%, (113 patients), DIPRIVAN 1%, (109 patients), or an SSA (e.g., lorazepam, chloral hydrate, fentanyl, ketamine, morphine, or phenobarbital). DIPRIVAN therapy was initiated at an infusion rate of 5.5 mg/kg/hr and titrated as needed to maintain sedation at a standardized level. The results of the study showed an increase in the number of deaths in patients treated with DIPRIVAN as compared to SSAs. Of the 25 patients who died during the trial or within the 28-day follow up period: 12 (11% were) in the DIPRIVAN 2% treatment group, 9 (8% were) in the DIPRIVAN 1% treatment group, and 4% were (4%) in the SSA treatment group. The differences in mortality rate between the groups were not statistically significant. Review of the deaths failed to reveal a correlation with underlying disease status or a correlation to the drug or a definitive pattern to the causes of death.

16 HOW SUPPLIED/STORAGE AND HANDLING

DIPRIVAN (propofol) injectable emulsion, USP is available as follows:

Product Code | Each | Unit of Sale | Strength
NP260910 | NDC 63323-269-06 10 mL ready-to-use single-dose vial for single patient use only. | NDC 63323-269-16 Packages of ten. | 100 mg per 10 mL (10 mg per mL)
NP260929 | NDC 63323-269-25 20 mL ready-to-use single-dose vial for single patient use only. | NDC 63323-269-37 Packages of ten. | 200 mg per 20 mL (10 mg per mL)
NP260957 | NDC 63323-269-23 50 mL ready-to-use single-dose vial for single patient use only. | NDC 63323-269-57 Packages of twenty. | 500 mg per 50 mL (10 mg per mL)
NP260967 | NDC 63323-269-21 100 mL ready-to-use single-dose vial for single patient use only. | NDC 63323-269-67 Packages of ten. | 1,000 mg per 100 mL vial (10 mg per mL)

Store between 4°C to 25°C (40°F to 77°F). Do not freeze. Shake well before use.

17 PATIENT COUNSELING INFORMATION

17.1 Impaired Mental Alertness

Advise patients that performance of activities requiring mental alertness, such as operating a motor vehicle or hazardous machinery or signing legal documents may be impaired for some time after general anesthesia or sedation.

17.2 Effect of Anesthetic and Sedation Drugs on Early Brain Development

Studies conducted in young animals and children suggest repeated or prolonged use of general anesthetic or sedation drugs in children younger than 3 years may have negative effects on their developing brains. Discuss with parents and caregivers the benefits, risks, and timing and duration of surgery or procedures requiring anesthetic and sedation drugs.

All trademarks are the property of Fresenius Kabi USA, LLC.

Novaplus is a registered trademark of Vizient, Inc.

Manufactured for:

Fresenius Kabi

Lake Zurich, IL 60047

www.fresenius-kabi.com/us

PACKAGE LABEL – PRINCIPAL DISPLAY – Diprivan® 10 mL Vial Label

NDC 63323-269-06

NP260910

DIPRIVAN® (Propofol) INJECTABLE EMULSION, USP

100 mg per 10 mL (10 mg per mL)

FOR INTRAVENOUS ADMINISTRATION

10 mL Single-Dose Vial

SHAKE WELL BEFORE USING

PACKAGE LABEL - PRINCIPAL DISPLAY - Diprivan® 10 mL Vial Carton Panel

NDC 63323-269-16

NP260910

DIPRIVAN® (Propofol) INJECTABLE EMULSION, USP

100 mg per 10 mL (10 mg per mL)

FOR INTRAVENOUS ADMINISTRATION

Ten 10 mL Vials

Single-Dose Vials

SHAKE WELL BEFORE USING

Rx only

PACKAGE LABEL - PRINCIPAL DISPLAY - Diprivan® 20 mL Vial Label

DIPRIVAN® (Propofol) INJECTABLE EMULSION, USP

200 mg per 20 mL (10 mg per mL)

FOR INTRAVENOUS ADMINISTRATION

20 mL Single-Dose Vial

SHAKE WELL BEFORE USING

PACKAGE LABEL - PRINCIPAL DISPLAY - Diprivan® 20 mL Vial Carton Panel

NDC 63323-269-37

NP260929

DIPRIVAN® (Propofol) INJECTABLE EMULSION, USP

200 mg per 20 mL (10 mg per mL)

FOR INTRAVENOUS ADMINISTRATION

SHAKE WELL BEFORE USING

Ten 20 mL vials

Single-Dose Vials

Sterile, nonpyrogenic

PACKAGE LABEL – PRINCIPAL DISPLAY – Diprivan® 50 mL Vial Label

NDC 63323-269-23 NP260957

DIPRIVAN® (Propofol) INJECTABLE EMULSION, USP

500 mg per 50 mL (10 mg per mL)

FOR INTRAVENOUS ADMINISTRATION

50 mL Single-Dose Vial

PACKAGE LABEL – PRINCIPAL DISPLAY – Diprivan® 50 mL Vial Carton Panel

NDC 63323-269-57 NP260957

DIPRIVAN® (Propofol) INJECTABLE EMULSION, USP

500 mg per 50 mL (10 mg per mL)

FOR INTRAVENOUS ADMINISTRATION

SHAKE WELL BEFORE USING

Twenty 50 mL Vials

Single-Dose Vials

Rx only

PACKAGE LABEL – PRINCIPAL DISPLAY – Diprivan® 100 mL Vial Label

NDC 63323-269-21 NP260967

DIPRIVAN® (Propofol) INJECTABLE EMULSION, USP

1000 mg per 100 mL (10 mg per mL)

FOR INTRAVENOUS ADMINISTRATION

100 mL Single-Dose Vial

SHAKE WELL BEFORE USING

Rx only

PACKAGE LABEL – PRINCIPAL DISPLAY – Diprivan® 100 mL Vial Carton Panel

NDC 63323-269-67 NP260967

DIPRIVAN® (Propofol) INJECTABLE EMULSION, USP

1000 mg per 100 mL (10 mg per mL)

FOR INTRAVENOUS ADMINISTRATION

SHAKE WELL BEFORE USING

Ten 100 mL Vials

Single-Dose Vials

Rx only